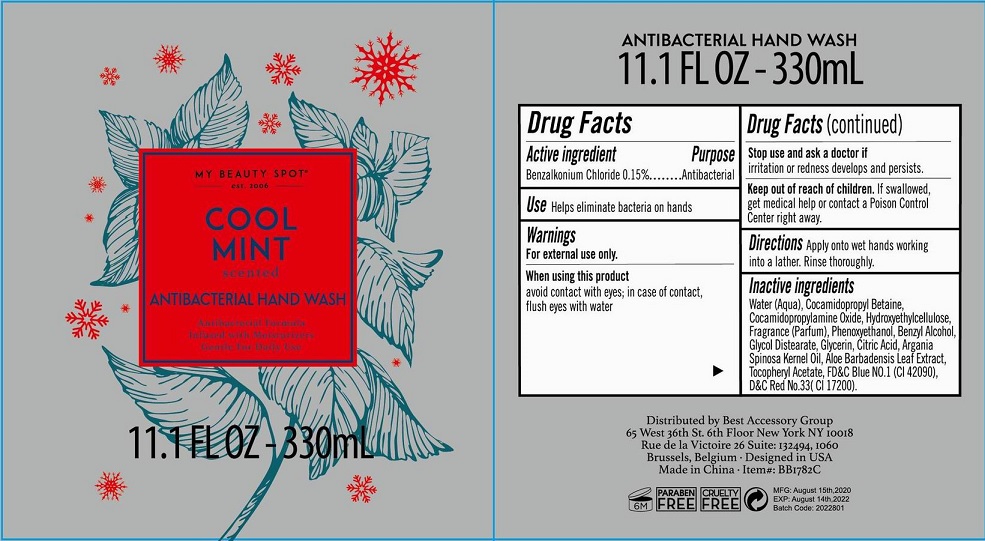 DRUG LABEL: Cool Mint Scented Antibacterial Hand Wash
NDC: 56136-208 | Form: LOTION
Manufacturer: Ganzhou Olivee Cosmetic Co., Ltd.
Category: otc | Type: HUMAN OTC DRUG LABEL
Date: 20200923

ACTIVE INGREDIENTS: BENZALKONIUM CHLORIDE 1.5 mg/1 mL
INACTIVE INGREDIENTS: WATER; COCAMIDOPROPYL BETAINE; COCAMIDOPROPYLAMINE OXIDE; BENZYL ALCOHOL; GLYCERIN; ACETYLTRIETHYL CITRATE; PHENOXYETHANOL; GLYCOL DISTEARATE; D&C RED NO. 33; FD&C BLUE NO. 1

hand wash

Active ingredient

Benzalkonium Chloride 0.15%

Purpose

Antibacterial

USE

Helps eliminate bacteria on hands

Warnings

For external use only.

When using this product

avoid contact with eyes; in case of contact, flush eyes with water.

Stop use and ask a doctor if

- irritation and redness develops and persists.

Keep out of reach of children.

If swallowed, get medical help or contact a Poison Control Center right away.

Directions

Apply onto wet hands working into a lather. Rinse thoroughly.

Inactive ingredients

Water (Aqua), Cocamidopropyl Betaine, Cocamidopropylamine Oxide, Hydroxethylcellulose, Fragrance (Parfum), Phenoxyethanol, Bezyl Alcohol, Glycerin, Glycol Distearate, Citric Acid, Argania Spinosa Kernel Oil, Tocopheryl Acetate, Aloe Barbadensis Leaf Extract, Tocopheryl Acetate, FD&C Blue No. 1 (CI 42090), D&C Red No. 33 (CI 17200).